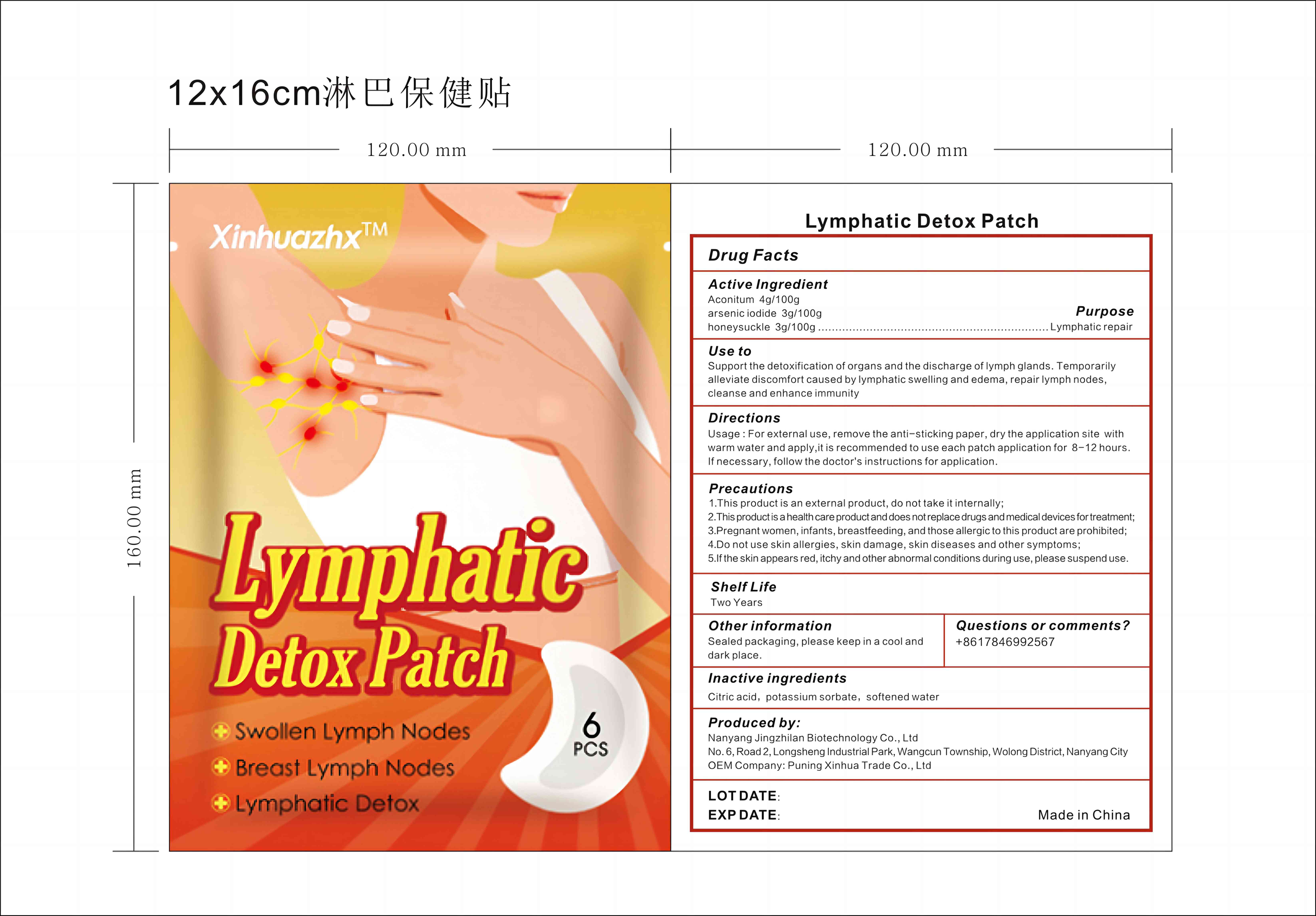 DRUG LABEL: Xinhuazhx Lymphatic Detox Patch
NDC: 83702-015 | Form: PATCH
Manufacturer: Puning Xinhua Trade Co., Ltd.
Category: otc | Type: HUMAN OTC DRUG LABEL
Date: 20231018

ACTIVE INGREDIENTS: LONICERA CAPRIFOLIUM FLOWER 3 g/100 g; ACONITUM CHASMANTHUM WHOLE 4 g/100 g; ARSENIC TRIIODIDE 3 g/100 g
INACTIVE INGREDIENTS: CITRIC ACID MONOHYDRATE; WATER; POTASSIUM SORBATE

Xinhuazhx Lymphatic Detox Patch 83702-015-12

Active ingredient: Aconitum 4g/100g，arsenic iodide 3g/100g，honeysuckle 3g/100g

Purpose: Lymphaticrepair

INDICATIONS AND USAGE

Use to
Support the detoxification of organs and the discharge of lymph glands. Temporarily alleviate discomfort caused by lymphatic swelling and edema, repair lymph nodes, cleanse and enhance immunity

Directions
Usage : For external use, remove the anti-sticking paper, dry the application site with warm water and apply,it is recommended to use each patch application for 8-12 hours. If necessary, follow the doctor's instructions for application.

WARNINGS

Precautions
1.This product is an external product, do not take it internally;
2.This product is a health care product and does not replace drugs and medical devices for treatment;
3.Pregnant women, infants, breastfeeding, and those allergic to this product are prohibited;
4.Do not use skin allergies, skin damage, skin diseases and other symptoms;
5.If the skin appears red, itchy and other abnormal conditions during use, please suspend use.

Questions or comments? +8617846992567

Inactive Ingredients: Citric acid, potassium sorbate, softened water

Other information: Sealed packaging, please keep in a cool and dark place.

Produced by:
Nanyang Jingzhilan Biotechnology Co., Ltd
No.6,Road2,Longsheng IndustrialPark,Wangcun Township, Wolong District,Nanyang City
OEM Company: Puning Xinhua Trade Co., Ltd

KEEP OUT OF REACH OF CHILDREN

Same as WARNINGS SECTION

Label